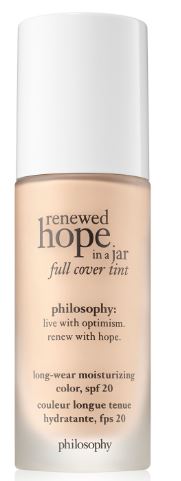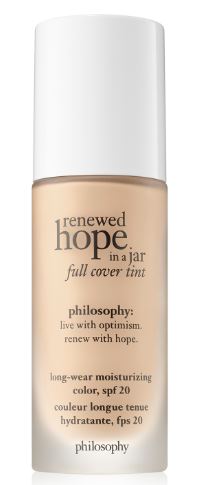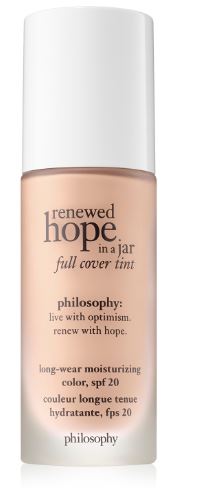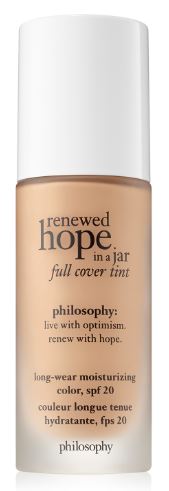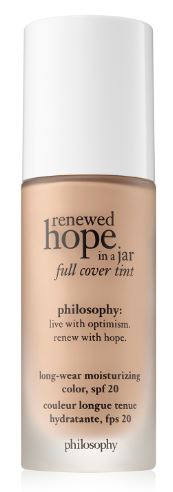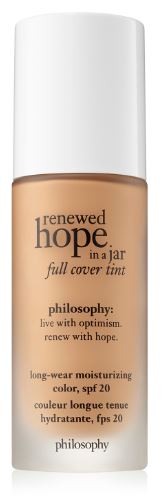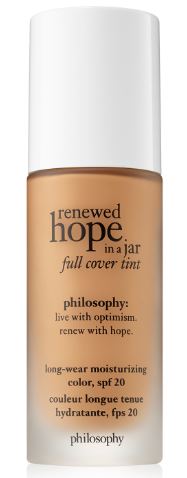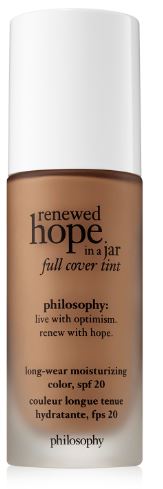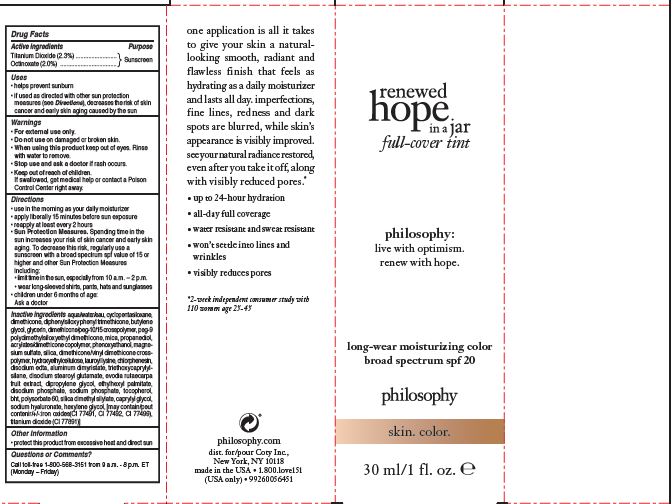 DRUG LABEL: renewed hope in a jar full cover tint spf 20
NDC: 50184-1064 | Form: LIQUID
Manufacturer: PHILOSOPHY, INC.
Category: otc | Type: HUMAN OTC DRUG LABEL
Date: 20200211

ACTIVE INGREDIENTS: OCTINOXATE 2 g/100 mL; TITANIUM DIOXIDE 2.3 g/100 mL
INACTIVE INGREDIENTS: MAGNESIUM SULFATE, UNSPECIFIED; LAUROYL LYSINE; CHLORPHENESIN; PEG-9 POLYDIMETHYLSILOXYETHYL DIMETHICONE; MICA; CAPRYLYL GLYCOL; DIPHENYLSILOXY PHENYL TRIMETHICONE; WATER; BUTYLENE GLYCOL; GLYCERIN; PROPANEDIOL; ALUMINUM DIMYRISTATE

renewed hope in a jar full cover tint spf 20

Active ingredients

Titanium Dioxide (2.3%)

Octinoxate (2.0%)

Purpose

Sunscreen

Uses

helps prevent sunburn

if used as directed with other sun protection measures (see Directions), decreases the risk of skin cancer and early skin aging caused by the sun.

Warnings

For external use only.

Do not use

on damaged or broken skin.

When using this product

keep out of eyes. RInse with water to remove.

Stop use and ask a doctor

if rash occurs.

Keep out of reach of children.

If swallowed, get medical help or contact a Posion Control Center right away.

Directions

use in the morning as your daily moisturizer

apply liberally 15 minutes before sun exposure

reapply at least every 2 hours

Sun Protection Measures. Spending time in the sun increases your risk of skin cancer and early skin aging. To decrease this risk, regularly use a sunscreen with a Broad Spectrum SPF value of 15 or higher and other sun protection measures including: [bullet] limit time in the sun, especially from 10 a.m.-2 p.m. [bullet] wear long-sleeved shirts, pants, hats, and sunglasses.

children under 6 months of age: Ask a doctor

Inactive ingredients

AQUA/WATER/EAU, CYCLOPENTASILOXANE, DIMETHICONE, DIPHENYLSILOXY PHENYL TRIMETHICONE, BUTYLENE GLYCOL, GLYCERIN, DIMETHICONE/PEG-10/15 CROSSPOLYMER, PEG-9 POLYDIMETHYLSILOXYETHYL DIMETHICONE, MICA, PROPANEDIOL, ACRYLATES/DIMETHICONE COPOLYMER, PHENOXYETHANOL, MAGNESIUM SULFATE, SILICA, DIMETHICONE/VINYL DIMETHICONE CROSSPOLYMER, HYDROXYETHYLCELLULOSE, LAUROYL LYSINE, CHLORPHENESIN, DISODIUM EDTA, ALUMINUM DIMYRISTATE, TRIETHOXYCAPRYLYLSILANE, DISODIUM STEAROYL GLUTAMATE, EVODIA RUTAECARPA FRUIT EXTRACT, DIPROPYLENE GLYCOL, ETHYLHEXYL PALMITATE, DISODIUM PHOSPHATE, SODIUM PHOSPHATE, TOCOPHEROL, BHT, POLYSORBATE 60, SILICA DIMETHYL SILYLATE, CAPRYLYL GLYCOL, SODIUM HYALURONATE, HEXYLENE GLYCOL, [May Contain/Peut Contenir/+/-:IRON OXIDES(CI 77491, CI 77492, CI 77499), TITANIUM DIOXIDE (CI 77891)]

Other information

protect this product from excessive heat and direct sun

Questions or Comments?

Call toll-free 1-800-568-3151 from 9 a.m.-8 p.m. ET (Monday-Friday)

PACKAGE LABEL

renewed

hope

in a jar

full-cover tint

philosophy:

live with optimism.

renew with hope.

long-wear moisturizing color

broad spectrum spf 20

philosophy

skin. color.